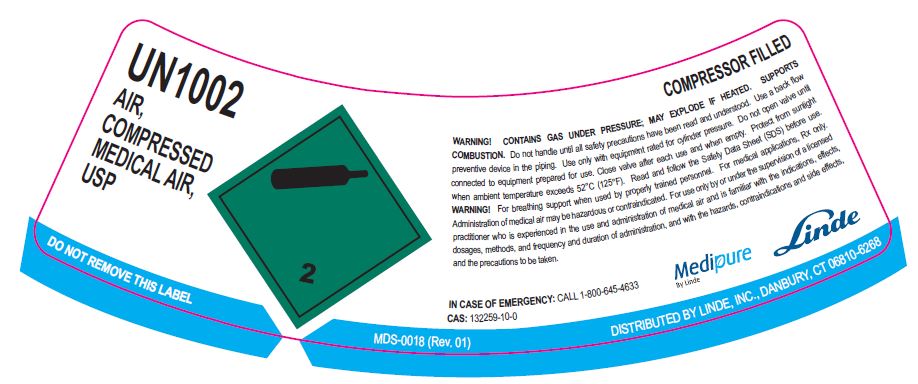 DRUG LABEL: Air
NDC: 59579-006 | Form: GAS
Manufacturer: Linde Gas & Equipment Inc.
Category: prescription | Type: HUMAN PRESCRIPTION DRUG LABEL
Date: 20250127

ACTIVE INGREDIENTS: AIR 1000 mL/1 L

Air-Human

PACKAGE LABEL

UN1002

AIR, COMPRESSED MEDICAL AIR, USP

COMPRESSOR FILLED

WARNING! CONTAINS GAS UNDER PRESSURE; MAY EXPLODE IF HEATED. SUPPORTS COMBUSTION. Do not handle until all safety precautions have been read and understood. Use a back flow preventative device in the piping. Use only with equipment rated for cylinder pressure. Do not open valve until connected to equipment prepared for use. Close valve after each use and when empty. Protect from sunlight when ambient temperature exceeds 52°C (125°F). Read and follow the Safety Data Sheet (SDS) before use.

Warning! For breathing support when used by properly trained personnel. For medical applications, Rx only.

Administration of medical air may be hazardous or contraindicated. For use only by or under the supervision of a licensed practitioner, who is experienced in the use and administration of medical air and is familiar with the indications, effects, dosages, methods and frequency and duration of adminisation, and with the hazards, contraindications and side effects, and the precautions to be taken.

IN CASE OF EMERGENCY: CALL 1-800-645-4633

CAS: 132259-10-0

Medipure by Linde

Linde

DO NOT REMOVE THIS LABEL MDS-0018 (Rev. 01) DISTRIBUTED BY LINDE, INC., DANBURY, CT 06810-6268